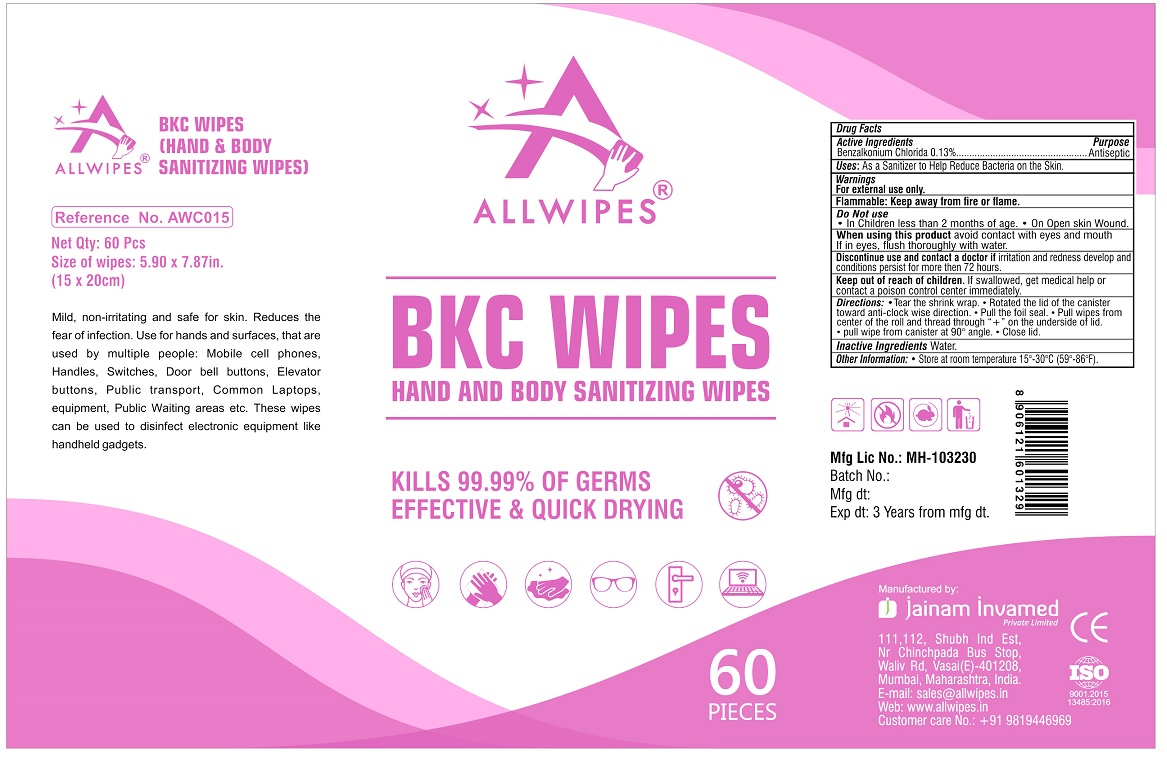 DRUG LABEL: ALLWIPES
NDC: 81297-101 | Form: CLOTH
Manufacturer: JAINAM INVAMED PRIVATE LIMITED
Category: otc | Type: HUMAN OTC DRUG LABEL
Date: 20201223

ACTIVE INGREDIENTS: BENZALKONIUM CHLORIDE 0.13 g/100 mL
INACTIVE INGREDIENTS: WATER

ALLWIPES® BKC WIPES

Active Ingredients

Benzalkonium Chloride 0.13%

Purpose

Antiseptic

Uses:

As a Sanitizer to Help Reduce Bacteria on the Skin.

Warnings

For external use only.

Flammable: Keep away from fire or flame.

Do Not Use

• In Children in less than 2 months of age. • On Open skin Wound.

When using this product avoid contact with eyes and mouth. If in eyes, flush thoroughly with water.

Discontinue use and contact a doctor if irritation and redness develop and conditions persist for more than 72 hours.

Keep out of reach of children. If swallowed, get medical help or contact a poison control center immediately.

Directions:

• Tear the shrink wrap. • Rotated the lid of the canister toward anti-clock wise direction. • Pull the foil seal. • Pull wipes from center of the roll and thread through "+" on the underside of the lid. • Pull wipe from canister at 90° angle. • Close lid.

Inactive Ingredients

Water.

Other Information:

- Store at room temperature 15°-30°C (59°-86°F).

HAND AND BODY SANITIZING WIPES

KILLS 99.99% OF GERMS

EFFECTIVE & QUICK DRYING

Mild, non-irritating and safe for skin. Reduces the fear of infection. Use for hands and surfaces, that are used by multiple people: Mobile cell phones, Handles, Switches, Door bell buttons, Elevator buttons, Public transport, Common Laptops, equipment, Public Waiting areas etc. These wipes can be used to disinfect electronic equipment like handheld gadgets.

Manufactured by:

jainam invamed Private Limited

111,112, Shubh Ind Est,

Nr Chinchpada Bus Stop,

Waliv Rd, Vasai(E)-401208,

Mumbai, Maharashtra, India.

E-mail: sales@allwipes.in

Web: www.allwipes.in

Customer care No.: +91 9819446969

ISO 9001.2015

13485:2016